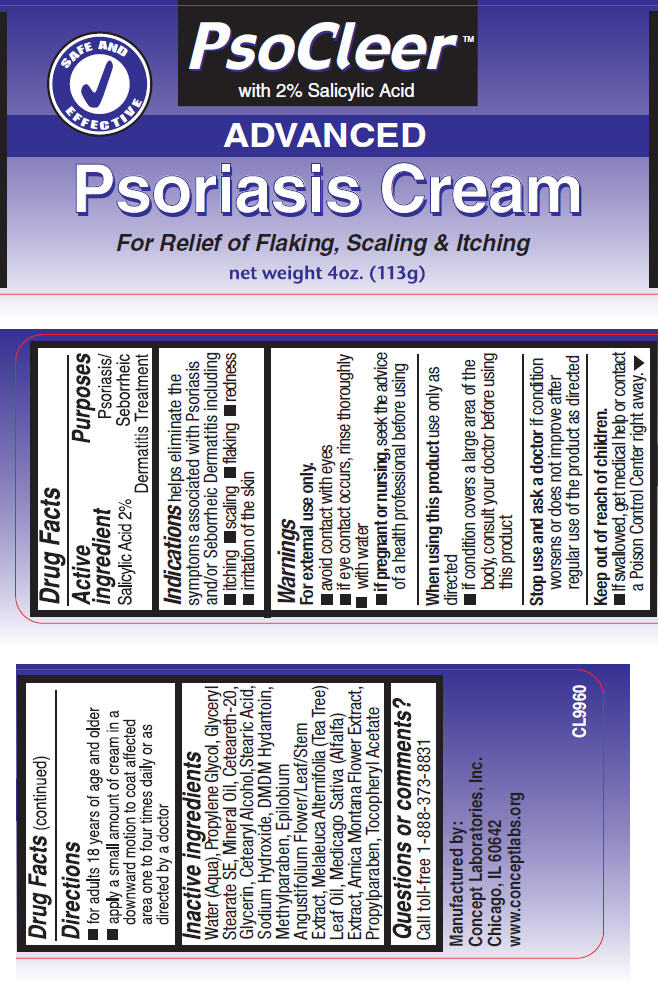 DRUG LABEL: PsoCleer 
NDC: 64058-211 | Form: CREAM
Manufacturer: Concept Laboratories, Inc.
Category: otc | Type: HUMAN OTC DRUG LABEL
Date: 20130425

ACTIVE INGREDIENTS: Salicylic Acid 2.26 g/113 g
INACTIVE INGREDIENTS: Water; Glycerin; GLYCERYL MONOSTEARATE; MINERAL OIL; STEARIC ACID; ARNICA MONTANA FLOWER; ALFALFA LEAF; EPILOBIUM ANGUSTIFOLIUM FLOWERING TOP; SODIUM HYDROXIDE; DMDM HYDANTOIN; PROPYLENE GLYCOL; METHYLPARABEN; PROPYLPARABEN

PsoCleer™
Advanced Psoriasis

Drug Facts

Active Ingredient

Salicylic Acid 2%

Purpose

Psoriasis/Seborrheic Dermatitis Treatment

Indications

Helps eliminate the symptoms associated with Psoriasis and/or Seborrheic Dermatitits including itching, scaling, flaking, redness, irritation of the skin

Warnings

For external use only

Avoid contact with eyes

If eye contact occurs, rinse thoroughly with water

PREGNANCY OR BREAST FEEDING

If pregnant or nursing, seek the advice of a health professional before using

When using this product use only as directed

ASK DOCTOR

If condition covers a large area of the body, consult your doctor before using this product

Stop use and ask a doctor if condition worsens or does not improve after regular use of the product as directed

Keep out of reach of children.

If swallowed, get medical help or contact a Poison Control Center right away.

Directions

For Adults 18 years of age and older

Apply a small amount of cream in a downward motion to coat affected area one to four times daily or as directed by a doctor.

Inactive ingredients

Water (Aqua), Propylene Glycol, Glyceryl Stearate SE, Mineral Oil, Ceteareth-20, Glycerin, Cetearyl Alcohol, Stearic Acid, Sodium Hydroxide, DMDM Hydantoin, Methylparaben, Epilobium Angustofolium Flower/Leaf/Stem Extract, Melaleuca Alternifolia (Alfalfa) Extract, Arnica Montana Flower Extract, Propylparaben, Tocopheryl Acetate.

Questions or Comments?

Call toll free 1-888-373-8831

Manufactured by:
Concept Laboratories, Inc.
Chicago, IL 60642
www.conceptlabs.org

CL 9960

PRINCIPAL DISPLAY PANEL - 113g Bottle Label

SAFE AND
EFFECTIVE

PsoCleer™
with 2% Salicylic Acid

ADVANCED

Psoriasis Cream

For Relief of Flaking, Scaling & Itching

net weight 4oz. (113g)